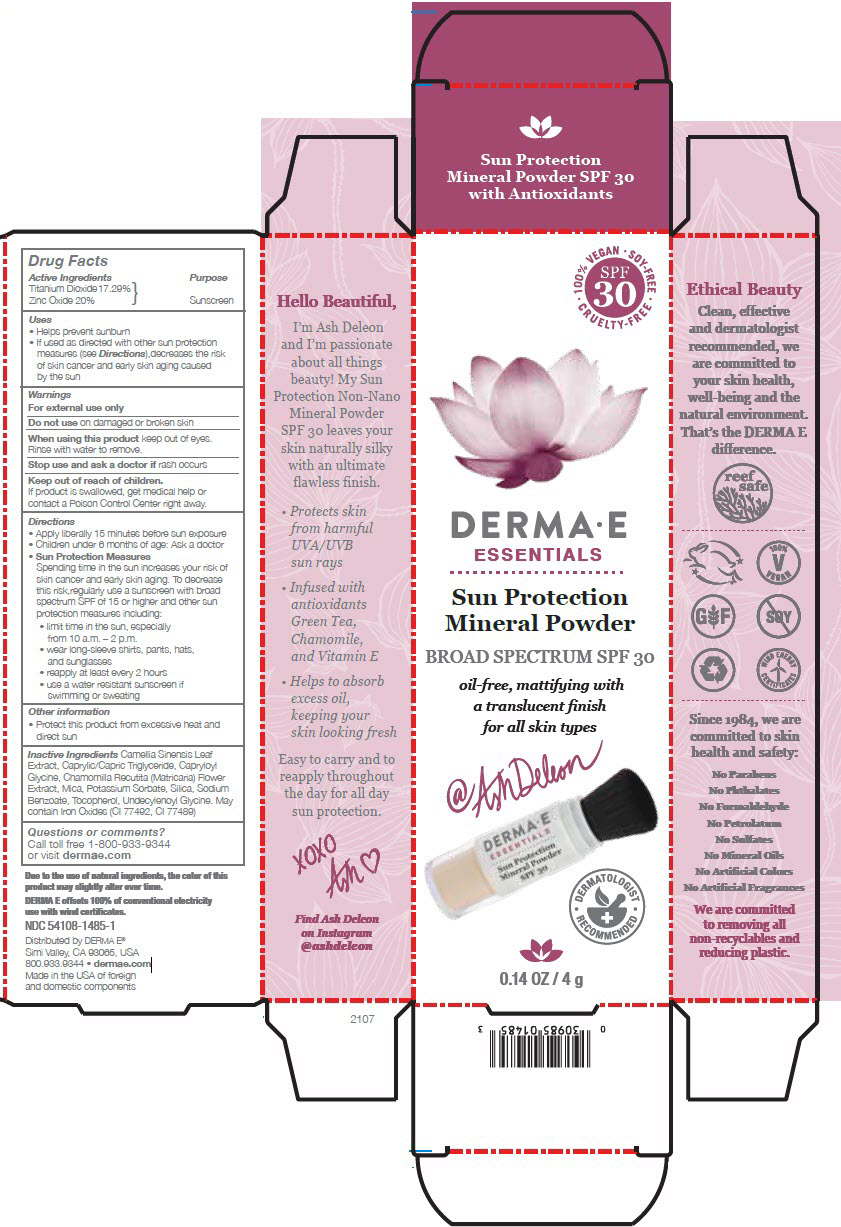 DRUG LABEL: Derma E Mineral sunscreen 
NDC: 54108-1485 | Form: POWDER
Manufacturer: derma e
Category: otc | Type: HUMAN OTC DRUG LABEL
Date: 20230130

ACTIVE INGREDIENTS: TITANIUM DIOXIDE 172.9 mg/1 g; ZINC OXIDE 200 mg/1 g
INACTIVE INGREDIENTS: GREEN TEA LEAF; MEDIUM-CHAIN TRIGLYCERIDES; SILICON DIOXIDE; MICA; POTASSIUM SORBATE; SODIUM BENZOATE; .ALPHA.-TOCOPHEROL; MATRICARIA CHAMOMILLA FLOWERING TOP OIL; CAPRYLOYL GLYCINE; UNDECYLENOYL GLYCINE; BROWN IRON OXIDE; FERRIC OXIDE YELLOW

Derma E Mineral Sunscreen
Mineral

Drug Facts

Active Ingredients

Titanium Dioxide 17.29%
Zinc Oxide 20%

Purpose

Sunscreen

Uses

- Helps prevent sunburn
- If used as directed with other sun protection measures (see Directions),decreases the risk of skin cancer and early skin aging caused by the sun

Warnings

For external use only

Do not use on damaged or broken skin

When using this product keep out of eyes. Rinse with water to remove.

Stop use and ask a doctor if rash occurs

Keep out of reach of children.

If product is swallowed, get medical help or contact a Poison Control Center right away.

Directions

- Apply liberally 15 minutes before sun exposure
- Children under 6 months of age: Ask a doctor
- Sun Protection Measures
  Spending time in the sun increases your risk of skin cancer and early skin aging. To decrease this risk,regularly use a sunscreen with broad spectrum SPF of 15 or higher and other sun protection measures including:
  - limit time in the sun, especially from 10 a.m. – 2 p.m.
  - wear long-sleeve shirts, pants, hats, and sunglasses
  - reapply at least every 2 hours
  - use a water resistant sunscreen if swimming or sweating

Other information

- Protect this product from excessive heat and direct sun

Inactive Ingredients

Camellia Sinensis Leaf Extract, Caprylic/Capric Triglyceride, Capryloyl Glycine, Chamomilla Recutita (Matricaria) Flower Extract, Mica, Potassium Sorbate, Silica, Sodium Benzoate, Tocopherol, Undecylenoyl Glycine. May contain Iron Oxides (CI 77492, CI 77489)

Questions or comments?

Call toll free 1-800-933-9344 or visit dermae.com

Distributed by DERMA E®
Simi Valley, CA 93065, USA

PRINCIPAL DISPLAY PANEL - 4 g Container Carton

100% VEGAN • SOY-FREE
• CRUELTY-FREE •
SPF
30

DERMA • E
ESSENTIALS

Sun Protection
Mineral Powder

BROAD SPECTRUM SPF 30

oil-free, mattifying with
a translucent finish
for all skin types

• DERMATOLOGIST
RECOMMENDED •

0.14 OZ / 4 g